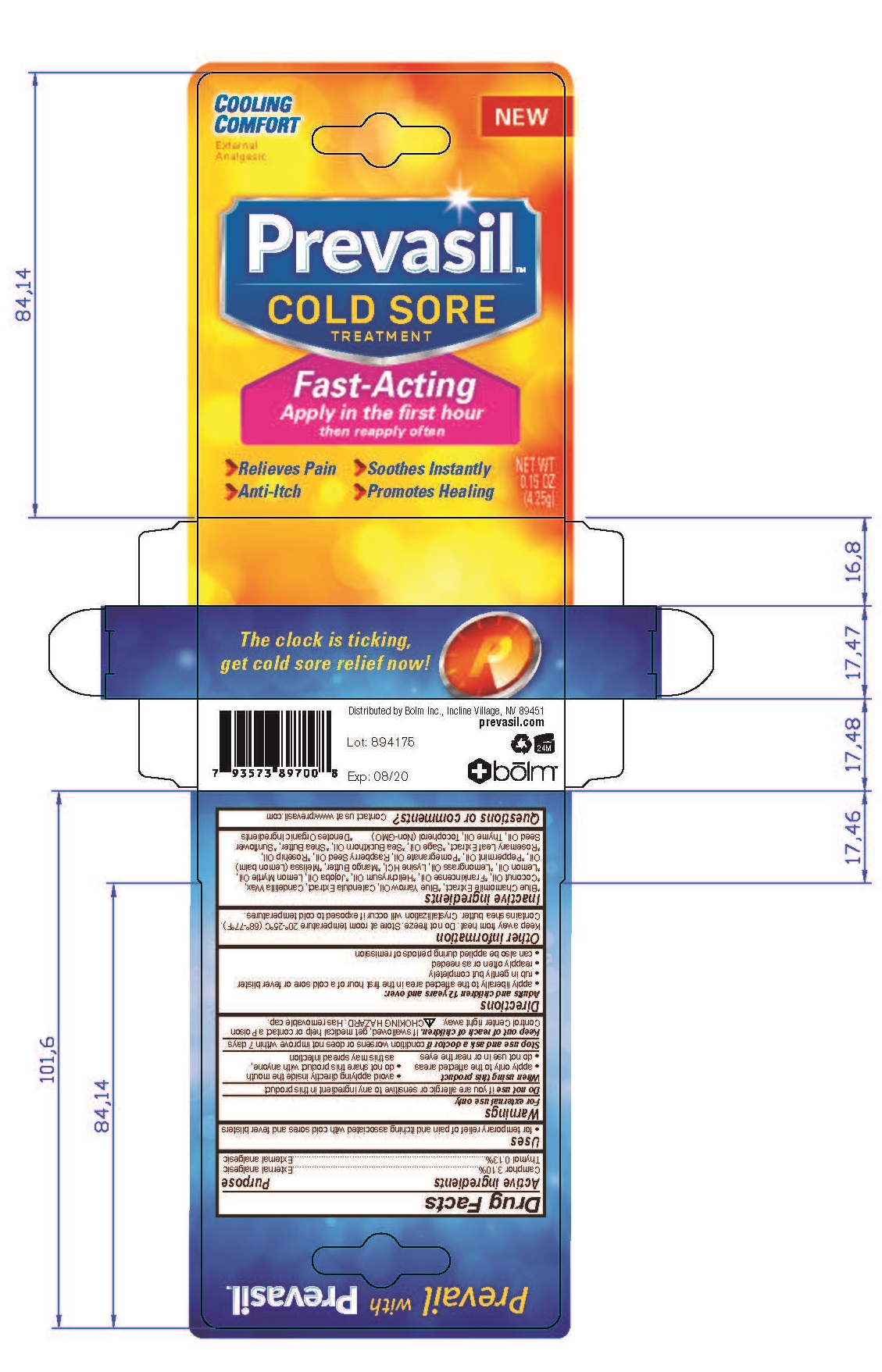 DRUG LABEL: Prevasil
NDC: 72456-001 | Form: GEL
Manufacturer: Bolm, Inc.
Category: otc | Type: HUMAN OTC DRUG LABEL
Date: 20180705

ACTIVE INGREDIENTS: CAMPHOR (SYNTHETIC) 31 mg/1 g; THYMOL 1.3 mg/1 g
INACTIVE INGREDIENTS: CHAMOMILE; ACHILLEA MILLEFOLIUM OIL; CALENDULA OFFICINALIS FLOWER; CANDELILLA WAX; COCONUT OIL; FRANKINCENSE OIL; HELICHRYSUM ITALICUM FLOWER OIL; JOJOBA OIL; BACKHOUSIA CITRIODORA LEAF OIL; LEMON OIL; EAST INDIAN LEMONGRASS OIL; LYSINE HYDROCHLORIDE; MANGIFERA INDICA SEED BUTTER; MELISSA OFFICINALIS LEAF OIL; PEPPERMINT OIL; Pomegranate Seed Oil; Raspberry Seed Oil; ROSA MOSCHATA OIL; ROSEMARY; SAGE OIL; HIPPOPHAE RHAMNOIDES SEED OIL; SHEA BUTTER; SUNFLOWER OIL; THYME OIL; TOCOPHEROL

Active ingredients

Synthetic camphor- 3.10%

Thymol crystals 0.13%

Purpose

External Anagesic

Warnings

For external use only
Do not use if you are allergic or sensitive to any ingredient in this product
When using this product
• apply only to the affected areas
• do not use in or near the eyes

• avoid applying directly inside the mouth

• do not share this product with anyone, as this may spread infection

Uses

Relieves Pain
Anti-Itch
Soothes Instantly
Promotes Healing
for temporary relief of pain and itching associated with cold sores and fever blisters

Stop use and ask a doctor if condition worsens or does not improve within 7 days

Keep out of reach of children. If swallowed, get medical help or contact a Poison
Control Center right away. CHOKING HAZARD. Has removable cap.

Directions

Adults and children 12 years and over:
• apply liberally to the affected area in the first hour of a cold sore or fever blister
• rub in gently but completely
• reapply often or as needed
• can also be applied during periods of remission

Storage

- Keep away from heat. Do not freeze. Store at room temperature 20o-25oC (68o-77oF)

Inactive Ingredients

*Blue Chamomile Extract, *Blue Yarrow Oil, Calendula Extract, Candelilla Wax,

*Coconut Oil, *Frankincense Oil, *Helichrysum Oil, *Jojoba Oil, Lemon Myrtle Oil,

*Lemon Oil, *Lemongrass Oil, Lysine HCl, *Mango Butter, *Melissa (Lemon balm)

Oil, *Peppermint Oil, *Pomegranate Oil, Raspberry Seed Oil, *Rosehip Oil,

*Rosemary Leaf Extract, *Sage Oil, *Sea Buckthorn Oil, *Shea Butter, *Sunflower

Seed Oil, Thyme Oil, Tocopherol (Non-GMO)

*Denotes Organic Ingredients

Questions or comments?

Contact us at www.prevasil.com